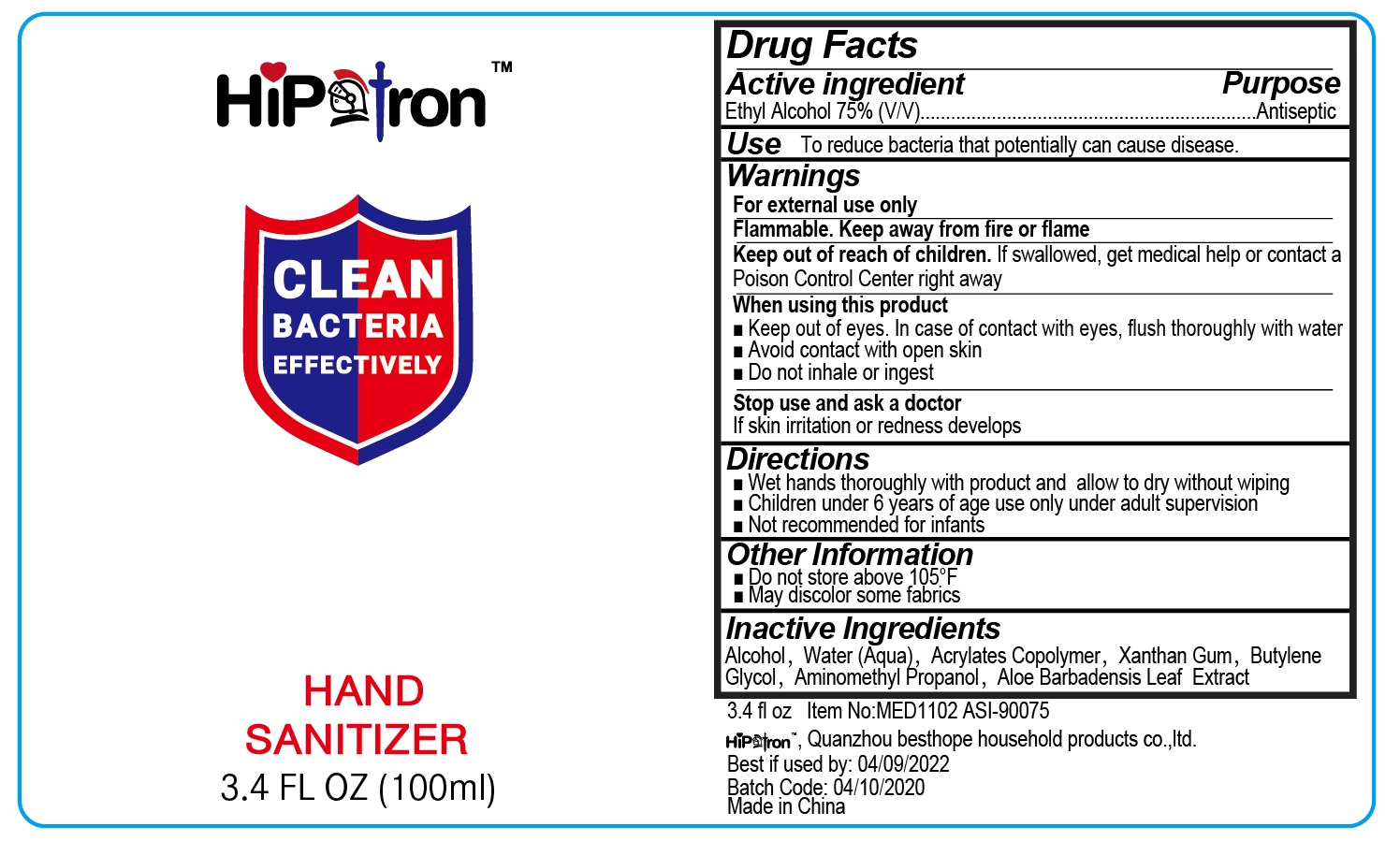 DRUG LABEL: Hand Sanitizer
NDC: 50049-002 | Form: GEL
Manufacturer: QUANZHOU BESTHOPE HOUSEHOLD PRODUCTS CO., LTD.
Category: otc | Type: HUMAN OTC DRUG LABEL
Date: 20200508

ACTIVE INGREDIENTS: ALCOHOL 75 mL/100 mL
INACTIVE INGREDIENTS: WATER; ALOE VERA LEAF; BUTYLENE GLYCOL; XANTHAN GUM; BUTYL ACRYLATE/METHYL METHACRYLATE/METHACRYLIC ACID COPOLYMER (18000 MW); AMINOMETHYL PROPANEDIOL

50049-002 Hand Sanitizer

Active ingredient

Ethyl Alcohol 75% v/v

Purpose

Antiseptic

Uses

To reduce bacteria that potentially can cause disease.

Warnings

For external use only
Flammable. Keep away from fire or flame
Keep out of reach of children. If swallowed, get medical help or contact a
Poison Control Center right away
When using this product
■Keep out of eyes. In case of contact with eyes, flush thoroughly with water
■Avoid contact with open skin
H Do not inhale or ingest
Stop use and ask a doctor
If skin irritation or redness develops

Keep out of reach of children. If swallowed, get medical help or contact a
Poison Control Center right away

Directions

■Wet hands thoroughly with product and allow to dry without wiping
■Children under 6 years of age use only under adult supervision
■Not recommended for infants

Other information

1 Do not store above 105°F
1 May discolor some fabrics

Inactive ingredients

Alcohol, Water (Aqua), Acrylates Copolymer, Xanthan Gum, Butylene
Glycol, Aminomethyl Propanol, Aloe Barbadensis Leaf Extract